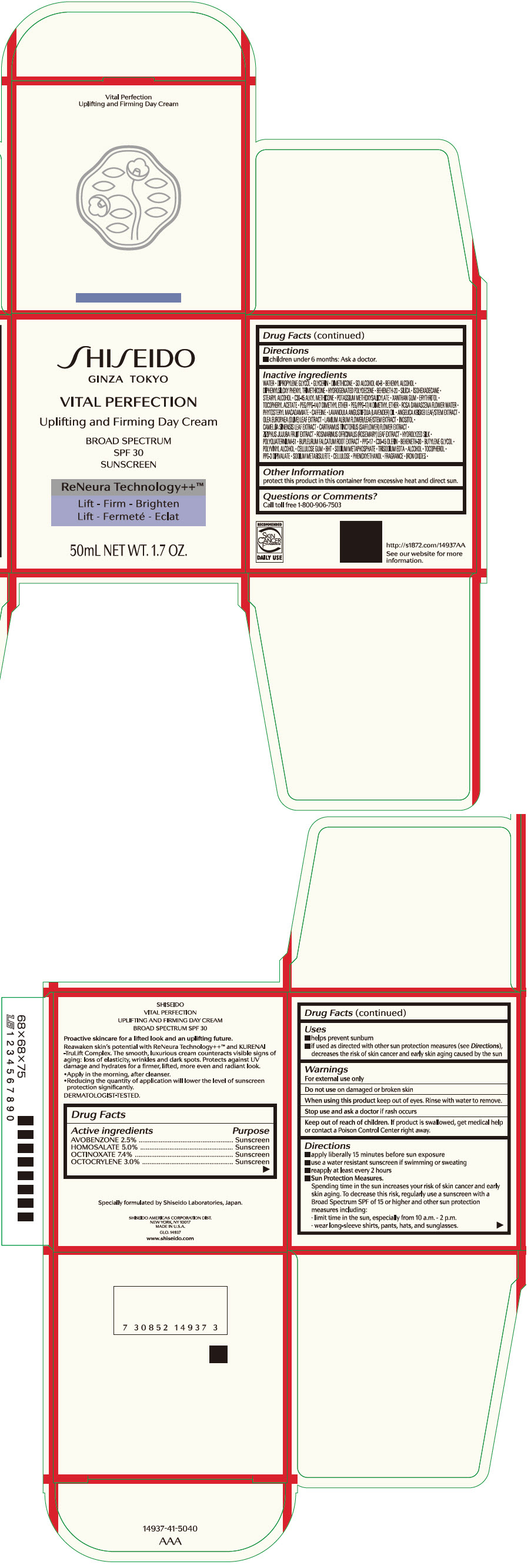 DRUG LABEL: SHISEIDO VITAL PERFECTION UPLIFTING AND FIRMING DAY
NDC: 58411-479 | Form: CREAM
Manufacturer: SHISEIDO AMERICAS CORPORATION
Category: otc | Type: HUMAN OTC DRUG LABEL
Date: 20260105

ACTIVE INGREDIENTS: AVOBENZONE 1.278 g/50 mL; OCTINOXATE 3.785 g/50 mL; OCTOCRYLENE 1.534 g/50 mL; HOMOSALATE 2.557 g/50 mL
INACTIVE INGREDIENTS: WATER; DIPROPYLENE GLYCOL; GLYCERIN; DIMETHICONE; DOCOSANOL; DIPHENYLSILOXY PHENYL TRIMETHICONE; HYDROGENATED POLYDECENE TYPE I; BEHENETH-20; SILICON DIOXIDE; ISOHEXADECANE; STEARYL ALCOHOL; C30-45 ALKYL METHICONE; POTASSIUM METHOXYSALICYLATE; XANTHAN GUM; ERYTHRITOL; .ALPHA.-TOCOPHEROL ACETATE, DL-; PEG/PPG-14/7 DIMETHYL ETHER; PEG/PPG-17/4 DIMETHYL ETHER; ROSA X DAMASCENA FLOWER OIL; PHYTOSTERYL MACADAMIATE; CAFFEINE; LAVENDER OIL; ANGELICA KEISKEI TOP; OLEA EUROPAEA LEAF; LAMIUM ALBUM FLOWERING TOP; INOSITOL; GREEN TEA LEAF; SAFFLOWER; JUJUBE FRUIT; ROSEMARY; POLYQUATERNIUM-51 (2-METHACRYLOYLOXYETHYL PHOSPHORYLCHOLINE/N-BUTYL METHACRYLATE; 3:7); BUPLEURUM FALCATUM ROOT; PPG-17; C30-45 OLEFIN; BEHENETH-30; BUTYLENE GLYCOL; POLYVINYL ALCOHOL, UNSPECIFIED; CARBOXYMETHYLCELLULOSE SODIUM, UNSPECIFIED; BUTYLATED HYDROXYTOLUENE; SODIUM POLYMETAPHOSPHATE; EDETATE TRISODIUM; ALCOHOL; .ALPHA.-TOCOPHEROL; SODIUM METABISULFITE; .ALPHA.-CELLULOSE; PHENOXYETHANOL; FERRIC OXIDE RED; FERRIC OXIDE YELLOW; FERROSOFERRIC OXIDE

SHISEIDO VITAL PERFECTION UPLIFTING AND FIRMING DAY CREAM

Drug Facts

ACTIVE INGREDIENT

Active ingredients | Purpose
Avobenzone 2.5% | Sunscreen
Octinoxate 7.4% | Sunscreen
Octocrylene 3.0% | Sunscreen
Homosalate 5.0% | Sunscreen

Uses

- helps prevent sunburn
- if used as directed with other sun protection measures (see Directions), decreases the risk of skin cancer and early skin aging caused by the sun

Warnings

For external use only

Do not use on damaged or broken skin

WHEN USING

When using this productkeep out of eyes. Rinse with water to remove.

Stop use and ask a doctorif rash occurs.

Keep out of reach of children.If product is swallowed, get medical help or contact a Poison Control Center right away.

Directions

- apply liberally 15 minutes before sun exposure
- use a water resistant sunscreen if swimming or sweating
- reapply at least every 2 hours
- children under 6 months: ask a doctor
- Sun Protection Measures. Spending time in the sun increases your risk of skin cancer and early skin aging. To decrease this risk, regularly use a sunscreen with a broad spectrum SPF of 15 or higher and other sun protection measures including:
  - limit time in the sun, especially from 10 a.m. – 2 p.m.
  - wear long-sleeve shirts, pants, hats, and sunglasses

Inactive Ingredients

WATER▪DIPROPYLENE GLYCOL▪GLYCERIN▪DIMETHICONE▪SD ALCOHOL 40-B▪BEHENYL ALCOHOL▪DIPHENYLSILOXY PHENYL TRIMETHICONE▪HYDROGENATED POLYDECENE▪;BEHENETH-20▪SILICA▪ISOHEXADECANE▪STEARYL ALCOHOL▪C30-45 ALKYL METHICONE▪POTASSIUM METHOXYSALICYLATE▪XANTHAN GUM▪ERYTHRITOL▪TOCOPHERYL ACETATE▪PEG/PPG-14/7 DIMETHYL ETHER▪PEG/PPG-17/4 DIMETHYL ETHER▪ROSA DAMASCENA FLOWER WATER▪PHYTOSTERYL MACADAMIATE▪CAFFEINE▪LAVANDULA ANGUSTIFOLIA (LAVENDER) OIL▪ANGELICA KEISKEI LEAF/STEM EXTRACT▪OLEA EUROPAEA (OLIVE) LEAF EXTRACT▪LAMIUM ALBUM FLOWER/LEAF/STEM EXTRACT▪INOSITOL▪CAMELLIA SINENSIS LEAF EXTRACT▪CARTHAMUS TINCTORIUS (SAFFLOWER) FLOWER EXTRACT▪ZIZIPHUS JUJUBA FRUIT EXTRACT▪ROSMARINUS OFFICINALIS (ROSEMARY) LEAF EXTRACT▪HYDROLYZED SILK▪POLYQUATERNIUM-51▪BUPLEURUM FALCATUM ROOT EXTRACT▪PPG-17▪C30-45 OLEFIN▪BEHENETH-30▪BUTYLENE GLYCOL▪POLYVINYL ALCOHOL▪CELLULOSE GUM▪BHT▪SODIUM METAPHOSPHATE▪TRISODIUM EDTA▪ALCOHOL▪TOCOPHEROL▪PPG-3 DIPIVALATE▪SODIUM METABISULFITE▪CELLULOSE▪PHENOXYETHANOL▪FRAGRANCE▪IRON OXIDES▪

Other information

Protect this product in this container from excessive heat and direct sun.

Questions or comments?

Call toll free 1-800-906-7503

PRINCIPAL DISPLAY PANEL - 50 mL Jar Carton

SHISEIDO
GINZA TOKYO

VITAL PERFECTION
Uplifting and Firming Day Cream

BROAD SPECTRUM
SPF 30
SUNSCREEN

ReNeura Technology++™
Lift - Firm - Brighten

50mL NET WT. 1.7 OZ.